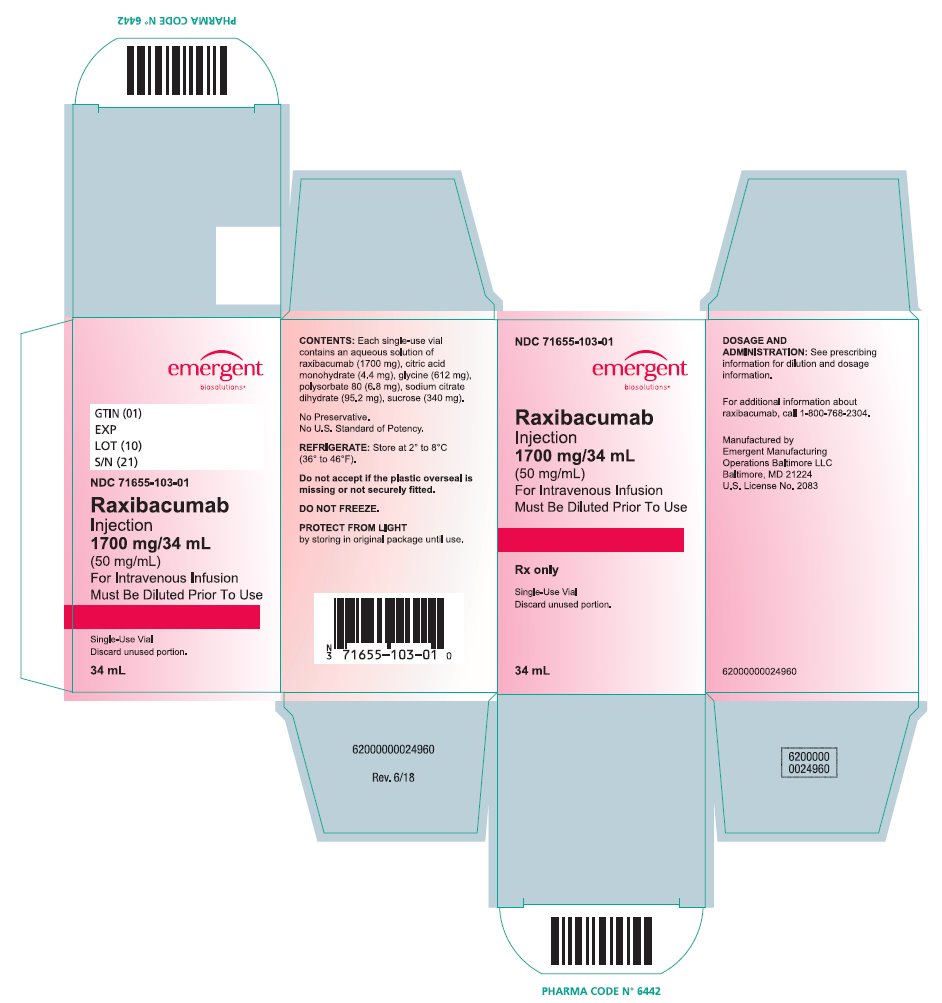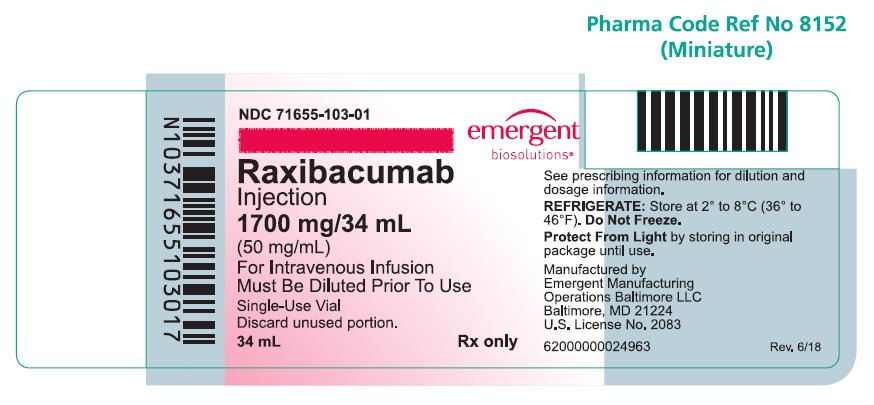 DRUG LABEL: Raxibacumab
NDC: 71655-103 | Form: INJECTION
Manufacturer: Emergent Manufacturing Operations Baltimore LLC
Category: prescription | Type: HUMAN PRESCRIPTION DRUG LABEL
Date: 20250110

ACTIVE INGREDIENTS: RAXIBACUMAB 50 mg/1 mL
INACTIVE INGREDIENTS: CITRIC ACID MONOHYDRATE; GLYCINE; POLYSORBATE 80; SODIUM CITRATE, UNSPECIFIED FORM; SUCROSE

HIGHLIGHTS OF PRESCRIBING INFORMATION

These highlights do not include all the information needed to use RAXIBACUMAB safely and effectively. See full prescribing information for RAXIBACUMAB.
RAXIBACUMAB injection, for intravenous use
Initial U.S. Approval: 2012

RECENT MAJOR CHANGES

Boxed Warning

Warnings and Precaution, Hypersensitivity and Anaphylaxis (5.1)

5/2021

5/2021

WARNING: HYPERSENSITIVITY and ANAPHYLAXIS

See full prescribing information for complete boxed warning

- Hypersensitivity reactions, including anaphylaxis, have been reported during or after the administration of raxibacumab by intravenous infusion (5.1).
- Administer raxibacumab by intravenous infusion in monitored settings where appropriate equipment, medication (including epinephrine) and personnel trained in the management of hypersensitivity, anaphylaxis, and shock are available (2.3, 5.1).

1 INDICATIONS AND USAGE

Raxibacumab is indicated for the treatment of adult and pediatric patients with inhalational anthrax due to Bacillus anthracisin combination with appropriate antibacterial drugs, and for prophylaxis of inhalational anthrax when alternative therapies are not available or are not appropriate. (1.1)

Limitations of Use:

- The effectiveness of raxibacumab is based solely on efficacy studies in animal models of inhalational anthrax. (1.2, 14.1)
- There have been no studies of raxibacumab in the pediatric population. Dosing in pediatric patients was derived using an extrapolation approach. (1.2, 8.4)
- Raxibacumab does not cross the blood-brain barrier and does not prevent or treat meningitis. Raxibacumab should be used in combination with appropriate antibacterial drugs. (1.2)

2 DOSAGE AND ADMINISTRATION

- Premedicate with diphenhydramine. (2.1, 2.2, 5.1)
- Dilute and administer as an intravenous infusion over 2 hours and 15 minutes. (2.3)
- - Adults: 40 mg/kg raxibacumab. (2.1)
- - Pediatrics greater than 40 kg: 40 mg/kg raxibacumab. (2.2)
- - Pediatrics greater than 10 kg to 40 kg: 60 mg/kg raxibacumab. (2.2)
- - Pediatrics 10 kg or less: 80 mg/kg raxibacumab. (2.2)

3 DOSAGE FORMS AND STRENGTHS

Injection: 1,700 mg/34 mL (50 mg/mL) solution in a single-use vial. (3)

4 CONTRAINDICATIONS

None. (4)

5 WARNINGS AND PRECAUTIONS

Hypersensitivity and Anaphylaxis: (Boxed Warning, 2.1, 2.3, 5.1, 6.1)

6 ADVERSE REACTIONS

Common adverse reactions in healthy adult subjects (≥1.5%) were injection site reaction, erythema and pain, headache, rash, pain in extremity, pruritus, and somnolence. (6.1)

To report SUSPECTED ADVERSE REACTIONS, contact Emergent BioSolutions at 1-800-768-2304 or FDA at 1-800-FDA-1088 or www.fda.gov/medwatch.

8 USE IN SPECIFIC POPULATIONS

Pediatric Use: Safety and effectiveness have not been studied in the pediatric population. (8.4)

FULL PRESCRIBING INFORMATION

WARNING: HYPERSENSITIVITY and ANAPHYLAXIS

- Hypersensitivity reactions, including anaphylaxis, have been reported during or after the administration of raxibacumab by intravenous infusion [see Warnings and Precautions (5.1)] .
- Administer raxibacumab by intravenous infusion in monitored settings where appropriate equipment, medication (including epinephrine) and personnel trained in the management of hypersensitivity, anaphylaxis, and shock are available [see Warnings and Precautions (2.3, 5.1)] .

1 INDICATIONS AND USAGE

1.1 Inhalational Anthrax

Raxibacumab is indicated for the treatment of adult and pediatric patients with inhalational anthrax due to Bacillus anthracisin combination with appropriate antibacterial drugs. Raxibacumab is also indicated for prophylaxis of inhalational anthrax when alternative therapies are not available or are not appropriate.

1.2 Limitations of Use

The effectiveness of raxibacumab is based solely on efficacy studies in animal models of inhalational anthrax. It is not ethical or feasible to conduct controlled clinical trials with intentional exposure of humans to anthrax [see Clinical Studies (14.1)].

Safety and pharmacokinetics (PK) of raxibacumab have been studied in adult healthy volunteers. There have been no trials of safety or PK of raxibacumab in the pediatric population. An extrapolation approach was used to derive dosing regimens that are predicted to provide pediatric patients with exposure comparable to the observed exposure in adults [see Use in Specific Populations (8.4)].

Raxibacumab binds to the protective antigen (PA) of B. anthracis; it does not have direct antibacterial activity. Raxibacumab does not cross the blood-brain barrier and does not prevent or treat meningitis. Raxibacumab should be used in combination with appropriate antibacterial drugs.

2 DOSAGE AND ADMINISTRATION

2.1 Dose and Schedule for Adults

Administer raxibacumab as a single dose of 40 mg/kg intravenously over 2 hours and 15 minutes after dilution in 0.9% Sodium Chloride Injection, USP (normal saline) to a final volume of 250 mL. Administer 25 to 50 mg diphenhydramine within 1 hour prior to the raxibacumab infusion to reduce the risk of occurrence and/or the severity of an infusion reaction. Diphenhydramine route of administration (oral or intravenous) should be based on the temporal proximity to the start of the raxibacumab infusion [see Warnings and Precautions (5.1) , Adverse Reactions (6.1)].

2.2 Dose and Schedule for Pediatric Patients

The recommended dose for pediatric patients is based on weight as shown in Table 1.

Table 1. Recommended Pediatric Dose
Pediatric Body Weight | Pediatric Dose
Greater than 40 kg | 40 mg/kg
Greater than 10 kg to 40 kg | 60 mg/kg
10 kg or less | 80 mg/kg

Premedicate with diphenhydramine within 1 hour prior to the raxibacumab infusion to reduce the risk of occurrence and/or the severity of an infusion reaction. Diphenhydramine route of administration (oral or intravenous) should be based on the temporal proximity to the start of the raxibacumab infusion. Infuse raxibacumab over 2 hours and 15 minutes. No pediatric patients were studied during the development of raxibacumab. The dosing recommendations in Table 1are derived from simulations designed to match the observed adult exposure to raxibacumab at a 40 mg/kg dose [see Use in Specific Populations (8.4)].

2.3 Preparation and Administration of Raxibacumab

The recommended dose of raxibacumab is weight-based, given as an intravenous infusion after dilution in a compatible solution to a final volume of 250 mL in adults or to a volume indicated based on the child’s weight (Table 2). Dilute raxibacumab using one of the following compatible solutions:

- 0.9% Sodium Chloride Injection, USP
- 0.45% Sodium Chloride Injection, USP

Keep vials in their cartons prior to preparation of an infusion solution to protect raxibacumab from light. Raxibacumab vials contain no preservative.

Table 2. Raxibacumab Dose, Diluents, Infusion Volumes, and Rates by Body Weight
 | Preparation |  |  | Administration
Body Weight | Dose | Total; Infusion; Volumea | Type of Diluent | Infusion Rate | Infusion Rate
Body Weight | Dose | Total; Infusion; Volumea | Type of Diluent | First 20 Minutes | Remaining Infusion
Adults
 | 40 mg/kg | 250 mL | 0.9% Sodium Chloride Injection | 15 mL/hour | 125 mL/hour
Pediatric Patients (Younger than 18 Years)
Less than 1 kg | 80 mg/kg | 7 mL | 0.45% Sodium Chloride Injection; or; 0.9% Sodium Chloride Injection | 0.5 mL/hour | 3.5 mL/hour
1 kg to less than 2 kg | 80 mg/kg | 15 mL | 0.45% Sodium Chloride Injection; or; 0.9% Sodium Chloride Injection | 1 mL/hour | 7 mL/hour
2 kg to less than 3 kg | 80 mg/kg | 20 mL | 0.45% Sodium Chloride Injection; or; 0.9% Sodium Chloride Injection | 1.2 mL/hour | 10 mL/hour
3 kg to less than 5 kg | 80 mg/kg | 25 mL | 0.45% Sodium Chloride Injection; or; 0.9% Sodium Chloride Injection | 1.5 mL/hour | 12 mL/hour
5 kg to 10 kg | 80 mg/kg | 40 mL | 0.45% Sodium Chloride Injection; or; 0.9% Sodium Chloride Injection | 3 mL/hour | 20 mL/hour
Greater than 10 kg to less than 15 kg | 60 mg/kg | 50 mL | 0.9% Sodium Chloride Injection | 6 mL/hour | 25 mL/hour
15 kg to less than 30 kg | 60 mg/kg | 100 mL | 0.9% Sodium Chloride Injection | 6 mL/hour | 50 mL/hour
30 kg to 40 kg | 60 mg/kg | 125 mL | 0.9% Sodium Chloride Injection | 15 mL/hour | 62.5 mL/hour
Greater than 40 kg | 40 mg/kg | 150 mL | 0.9% Sodium Chloride Injection | 15 mL/hour | 75 mL/hour
aFor patients requiring maximal fluid restriction, dilution factors can be adjusted at the discretion of the physician to a maximal concentration of 32 mg/mL.

Preparation

Follow the steps below to prepare the raxibacumab intravenous infusion solution.

1. Calculate the milligrams of raxibacumab injection by multiplying the recommended mg/kg dose in Table 2by patient weight in kilograms.
2. Calculate the required volume in milliliters of raxibacumab injection needed for the dose by dividing the calculated dose in milligrams (Step 1) by the concentration, 50 mg/mL. Each single-use vial allows delivery of 34 mL raxibacumab.

Based on the total infusion volume selected in Table 2, prepare either a syringe or infusion bag as appropriate following the steps below.

Syringe Preparation

1. Select an appropriate size syringe for the total volume of infusion to be administered, as described in Table 2.
2. Using the selected syringe, withdraw the volume of raxibacumab as calculated in Step 2.
3. Withdraw an appropriate amount of compatible solution to prepare a total volume infusion syringe as specified in Table 2.
4. Gently mix the solution. Do not shake.
5. Discard any unused portion remaining in the raxibacumab vial(s).
6. The prepared solution is stable for 8 hours stored at room temperature.

Infusion Bag Preparation

1. Select appropriate size bag of compatible solution (see compatible solutions listed in Table 2); withdraw a volume of solution from the bag equal to the calculated volume in milliliters of raxibacumab in Step 2 above. Discard the solution that was withdrawn from the bag.
2. Withdraw the required volume of raxibacumab injection from the raxibacumab vial(s).
3. Transfer the required volume of raxibacumab injection to the selected infusion bag (Step 3). Gently invert the bag to mix the solution. Do not shake.
4. Discard any unused portion remaining in the raxibacumab vial(s).
5. The prepared solution is stable for 8 hours stored at room temperature.

Parenteral drug products should be inspected visually for particulate matter and discoloration prior to administration, whenever solution and container permit. Discard the solution if particulate matter is present or color is abnormal [see Description (11)].

Administration

- Administer raxibacumab in monitored settings appropriately equipped to manage hypersensitivity, anaphylaxis, and shock [see Warnings and Precautions (5.1)] .
- Administer the infusion solution as described in Table 2. The rate of infusion may be slowed or interrupted if the patient develops any signs of adverse reactions, including infusion-associated symptoms.

3 DOSAGE FORMS AND STRENGTHS

Injection: 1,700 mg/34 mL (50 mg/mL) solution in a single-use vial.

4 CONTRAINDICATIONS

None.

5 WARNINGS AND PRECAUTIONS

5.1 Hypersensitivity and Anaphylaxis

Hypersensitivity reactions including rash, urticaria, pruritus, chills, chest and throat tightness, lip and throat swelling, and hypotension were reported in 27 (4.5%) of 606 healthy subjects during or after the administration of raxibacumab in clinical trials. Two subjects experienced anaphylaxis during the raxibacumab infusion [see Adverse Reactions (6.1)] .

Some subjects with hypersensitivity or anaphylaxis required interruption or discontinuation of the raxibacumab infusion as well as additional appropriate treatment that included steroids, diphenhydramine, H2 blockers, and/or intravenous fluids [see Adverse Reactions (6.1)] .

Due to the risk of anaphylaxis, administer raxibacumab injection in monitored settings where appropriate equipment, medication (including epinephrine) and personnel trained to manage hypersensitivity, anaphylaxis, and shock are available. Monitor patients closely during the infusion and for a period of time after administration. If hypersensitivity reactions or anaphylaxis occur, interrupt or stop the raxibacumab infusion immediately and treat appropriately.

Premedicate with diphenhydramine within 1 hour prior to administering raxibacumab to reduce the risk of occurrence and/or severity of a hypersensitivity reaction [see Dosage and Administration (2.1), Adverse Reactions (6.1)] . Diphenhydramine premedication does not prevent anaphylaxis and may mask or delay the onset of symptoms of hypersensitivity.

6 ADVERSE REACTIONS

6.1 Clinical Trials Experience

Because clinical trials are conducted under widely varying conditions, adverse reaction rates observed in the clinical trials of a drug cannot be directly compared with rates in the clinical trials of another drug and may not reflect the rates observed in practice. The safety of raxibacumab has been studied only in healthy volunteers. It has not been studied in patients with inhalational anthrax.

In the three pre-licensure clinical trials (Trials 1, 2, and 3), the safety of raxibacumab was evaluated in 326 healthy subjects treated with a dose of 40 mg/kg in 3 clinical trials: a drug interaction trial with ciprofloxacin (Trial 1), a repeat-dose trial of 20 subjects with the second raxibacumab dose administered ≥4 months after the first dose (Trial 2), and a placebo-controlled trial evaluating single doses with a subset of subjects receiving 2 raxibacumab doses 14 days apart (Trial 3). Raxibacumab was administered to 86 healthy subjects in Trial 1. In Trial 3, 240 healthy subjects received raxibacumab (217 received 1 dose and 23 received 2 doses) and 80 subjects received placebo.

The overall safety of raxibacumab was evaluated as an integrated summary of these 3 clinical trials. Of 326 raxibacumab subjects, 283 received single doses, 23 received 2 doses 14 days apart, and 20 received 2 doses more than 4 months apart. The subjects were aged 18 to 88 years, 53% female, 74% white, 17% black/African American, 6% Asian, and 15% Hispanic.

Trial 4 was a post-marketing trial in healthy subjects designed to evaluate the effect of a single 40 mg/kg infusion of raxibacumab on the immunogenicity of a concurrently administered 3-dose subcutaneous (SC) regimen of Anthrax Vaccine Adsorbed (AVA) [N=286] compared with an AVA-alone regimen [N=286]. In the combination arm, the first dose of AVA was administered immediately following the raxibacumab infusion (Day 1), while the second and third doses were administered on Days 15 and 29. The mean age of subjects was 36 years in both arms, 52% of subjects in the AVA arm and 50% in the AVA + raxibacumab arm were female, 75% and 77% in the two arms, respectively, were white, while 21% and 20%, respectively, were African American.

Adverse Reactions Leading to Discontinuation or Interruption of Raxibacumab Infusion

Four subjects (1.2%) in Trials 1, 2 and 3 had their infusion of raxibacumab discontinued for hypersensitivity and anaphylaxis: 2 subjects (neither of whom received diphenhydramine premedication) discontinued due to urticaria (mild), and 1 subject each discontinued for clonus (mild) and dyspnea (moderate).

In Trial 4, six (2.1%) subjects required discontinuation of the raxibacumab infusion and 3 (1.0%) subjects required infusion interruption due to hypersensitivity or anaphylaxis [see Warnings and Precautions (5.1)] .

Most Frequently Reported Adverse Reactions

Trials 1, 2, and -3

In Trials 1, 2, and 3, the most frequently reported adverse reactions were rash, pain in extremity, pruritus, and somnolence (Table 3).

Table 3. Adverse Reactions Reported in ≥1.5% of Healthy Adult Subjects Exposed to Raxibacumab 40 mg/kg Intravenously in Trials 1, 2, and 3
Adverse Reaction | Placebo; N = 80 (%) | Single-Dose Raxibacumab; N = 283 (%) | Double-Dose Raxibacumab; ≥4 Months Apart; N = 20 (%) | Double-Dose Raxibacumab; 2 Weeks Apart; N = 23 (%) | Total Raxibacumab Subjects; N = 326 (%)
Rash/Rash erythematous/Rash papular | 1 (1.3) | 9 (3.2) | 0 | 0 | 9 (2.8)
Pain in extremity | 1 (1.3) | 7 (2.5) | 0 | 0 | 7 (2.1)
Pruritus | 0 | 7 (2.5) | 0 | 0 | 7 (2.1)
Somnolence | 0 | 4 (1.4) | 0 | 1 (4.3) | 5 (1.5)

Rashes

For all subjects exposed to raxibacumab in Trials 1, 2, and 3, the rate of rash was 2.8% (9/326) compared with 1.3% (1/80) of placebo subjects. Mild to moderate infusion-related rashes were reported in 22.2% (6/27) of subjects who did not receive diphenhydramine premedication compared with 3.3% (2/61) of subjects who were premedicated with diphenhydramine in the ciprofloxacin/raxibacumab combination trial (Trial 1). In the placebo-controlled raxibacumab trial where all subjects received diphenhydramine (Trial 3), the rate of rash was 2.5% in both placebo- and raxibacumab-treated subjects.

Trial 4

Eleven (3.8%) of 286 subjects who received raxibacumab, all of whom received diphenhydramine premedication, experienced hypersensitivity manifesting as urticaria, pruritus, lip and throat swelling, chest and throat tightness, hypotension, and diffuse erythema; 2 (0.7%) of these subjects had anaphylaxis. Raxibacumab infusion was discontinued or interrupted in 9/11 subjects. Hypersensitivity reactions and anaphylaxis occurred during administration of raxibacumab prior to administration of the first dose of AVA [see Warnings and Precautions (5.1)] .

Common adverse reactions, other than hypersensitivity, occurring at a frequency of ≥1.5% in raxibacumab-exposed subjects are presented in Table 4.

Table 4. Adverse Reactions Other than Hypersensitivity Reported in ≥1.5% of Healthy Adult Subjects Exposed to Raxibacumab 40 mg/kg Intravenously in Trial 4
Adverse Reaction | AVA + Raxibacumab Subjects; N = 286 (%) | AVA Subjects; N = 286 (%)
Injection site reaction | 18 (6.3) | 18 (6.3)
Injection site erythema | 13 (4.5) | 11 (3.8)
Headache | 9 (3.1) | 6 (2.1)
Injection site pain | 8 (2.8) | 6 (2.1)

Less Common Adverse Reactions

Clinically significant adverse reactions that were reported in <1.5% of subjects exposed to raxibacumab and at rates higher than in placebo subjects are listed below:

- Blood and Lymphatic System Disorders:Anemia, leukopenia, lymphadenopathy.
- Cardiac Disorders:Palpitations.
- Ear and Labyrinth Disorders:Vertigo.
- General Disorders and Administration Site Conditions:Fatigue, infusion site pain, peripheral edema.
- Investigations:Blood amylase increased, blood creatine phosphokinase increased, prothrombin time prolonged.
- Musculoskeletal and Connective Tissue Disorders:Back pain, muscle spasms.
- Nervous System Disorders:Syncope.
- Psychiatric Disorders:Insomnia.
- Vascular Disorders:Flushing, hypertension.

Immunogenicity

The development of anti-raxibacumab antibodies was evaluated in all subjects receiving single and double doses of raxibacumab in Trials 1, 2, and 3. Immunogenic responses against raxibacumab were not detected in any raxibacumab-treated human subjects following single or repeat doses of raxibacumab.

The incidence of antibody formation is highly dependent on the sensitivity and specificity of the immunogenicity assay. Additionally, the observed incidence of any antibody positivity in an assay is highly dependent on several factors, including assay sensitivity and specificity, assay methodology, sample handling, timing of sample collection, concomitant medications, and underlying disease. For these reasons, comparison of the incidence of antibodies to raxibacumab with the incidence of antibodies to other products may be misleading.

7 DRUG INTERACTIONS

7.1 Ciprofloxacin

Co-administration of 40 mg/kg raxibacumab intravenously with intravenous or oral ciprofloxacin in human subjects did not alter the PK of either ciprofloxacin or raxibacumab [see Clinical Pharmacology (12.3)] .

7.2 Anthrax Vaccine Adsorbed (AVA)

Co-administration of 40 mg/kg raxibacumab intravenously (Day 1) with a SC AVA regimen (Days 1, 15, and 29) did not affect the immunogenicity of AVA [see Clinical Pharmacology (12.3)].

8 USE IN SPECIFIC POPULATIONS

8.1 Pregnancy

Risk Summary

There are no data on the use of raxibacumab in pregnant women to inform on drug-associated risk. In pregnant rabbits, intravenous administration of raxibacumab was not associated with teratogenicity or other adverse developmental outcomes at 3 times the human maximum plasma concentrations at the maximum recommended adult dose (see Data).

All pregnancies have a background risk of birth defect, loss, or other adverse outcomes. In the U.S. general population, the estimated background rate of major birth defects is 2% to 4% and of miscarriage is 15% to 20% of clinically recognized pregnancies.

Clinical Considerations

Disease-Associated Maternal and/or Embryo/Fetal Risk:Limited data in the form of case reports of anthrax infection in pregnant women indicate that maternal infection is associated with a high risk of maternal, fetal, and neonatal deaths, particularly in the absence of treatment.

Data

Animal Data:A study was conducted in pregnant, healthy New Zealand White rabbits administered intravenous raxibacumab at dose levels of 40 or 120 mg/kg on Gestation Days 7 and 14. No teratogenicity or other adverse developmental outcomes were observed in pregnant rabbits at 3 times the human maximum plasma concentrations at the maximum recommended adult dose of 40 mg/kg. Maternal toxicity was observed at both doses (reduced body weight gain late in gestation, but no difference in mean total weight gain).

8.2 Lactation

Risk Summary

There is no information available on the presence of raxibacumab in human milk, the effects on the breastfed child, or the effects on milk production. Maternal IgG is known to be present in human milk.

Therefore, the developmental and health benefits of breastfeeding should be considered along with the mother’s clinical need for raxibacumab and any potential adverse effects on the breastfed child from raxibacumab or from the underlying maternal condition.

8.4 Pediatric Use

As in adults, the effectiveness of raxibacumab in pediatric patients is based solely on efficacy studies in animal models of inhalational anthrax. As exposure of healthy children to raxibacumab is not ethical, an extrapolation approach was used to derive dosing regimens that are predicted to provide pediatric patients with exposure comparable to the observed exposure in adults receiving 40 mg/kg. The dose for pediatric patients is based on weight [see Dosage and Administration (2.2)].

Safety or PK of raxibacumab have not been studied in the pediatric population.

8.5 Geriatric Use

Clinical trials of raxibacumab did not include sufficient numbers of subjects aged 65 years and older to determine whether they respond differently from younger subjects. Of the total number of subjects in clinical trials of raxibacumab, 6.4% (21/326) were 65 years and older, while 1.5% (5/326) were 75 years and older. However, no alteration of dosing is needed for patients aged 65 years and older [see Clinical Pharmacology (12.3)].

10 OVERDOSAGE

There is no clinical experience with overdosage of raxibacumab. In case of overdosage, monitor patients for any signs or symptoms of adverse effects.

11 DESCRIPTION

Raxibacumab is a human IgG1λ monoclonal antibody that binds the PA component of B. anthracistoxin. Raxibacumab has a molecular weight of approximately 146 kilodaltons. Raxibacumab is produced by recombinant DNA technology in a murine cell expression system.

Raxibacumab is supplied as a sterile, preservative-free, clear to opalescent, colorless to pale yellow liquid formulation in single-use vials for intravenous infusion. Each vial contains 1,700 mg/34 mL (50 mg/mL) raxibacumab in citric acid (0.13 mg/mL), glycine (18 mg/mL), polysorbate 80 [0.2 mg/mL (w/v)], sodium citrate (2.8 mg/mL), sucrose (10 mg/mL), and Water for Injection, with a pH of 6.5.

12 CLINICAL PHARMACOLOGY

12.1 Mechanism of Action

Raxibacumab is a monoclonal antibody that binds the protective antigen of B. anthracis [see Microbiology (12.4)].

12.3 Pharmacokinetics

The PK of raxibacumab is linear over the dose range of 1 to 40 mg/kg following single intravenous dosing in humans; raxibacumab was not tested at doses higher than 40 mg/kg in humans. Following single intravenous administration of raxibacumab 40 mg/kg in healthy male and female human subjects, the mean Cmaxand AUCinfwere 1,020.3 ± 140.6 mcg/mL and 15,845.8 ± 4,333.5 mcg•day/mL, respectively. Mean raxibacumab steady-state volume of distribution was greater than plasma volume, suggesting some tissue distribution. Clearance values were much smaller than the glomerular filtration rate indicating that there is virtually no renal clearance of raxibacumab.

Because the effectiveness of raxibacumab cannot be tested in humans, a comparison of raxibacumab exposures achieved in healthy human subjects to those observed in animal models of inhalational anthrax in therapeutic efficacy studies is necessary to support the dosage regimen of 40 mg/kg intravenously as a single dose for the treatment of inhalational anthrax in humans. Humans achieve similar or greater systemic exposure (Cmaxand AUCinf) to raxibacumab following a single 40 mg/kg intravenous dose compared with New Zealand White rabbits and cynomolgus macaques receiving the same dosage regimen.

Effects of Gender, Age, and Race

Raxibacumab PK was evaluated via a population PK analysis using serum samples from 322 healthy subjects who received a single 40 mg/kg intravenous dose across 3 clinical trials. Based on this analysis, gender (female versus male), race (non-white versus white), or age (elderly versus young) had no meaningful effects on the PK parameters for raxibacumab.

Raxibacumab PK has not been evaluated in children [see Dosage and Administration (2.2), Use in Specific Populations (8.4)].

Repeat Dosing

Although raxibacumab is intended for single-dose administration, the PK of raxibacumab following a second administration of 40 mg/kg given intravenously 14 days after the first 40 mg/kg intravenous dose was assessed in 23 healthy subjects (Trial 3). The mean raxibacumab concentration at 28 days after the second dose was approximately twice the mean raxibacumab concentration at 14 days following the first dose. In the human trial assessing the immunogenicity of raxibacumab (Trial 2), 20 healthy subjects who had initially received a single dose of raxibacumab 40 mg/kg intravenously received a second 40 mg/kg intravenous dose at ≥4 months following their first dose. No statistically significant differences in mean estimates of AUCinf, CL, or half-life of raxibacumab between the 2 doses administered ≥4 months apart were observed. The mean Cmaxfollowing the second dose was 15% lower than the Cmaxfollowing the first dose.

Ciprofloxacin Interaction Trial

In an open-label trial evaluating the effect of raxibacumab on ciprofloxacin PK in healthy adult male and female subjects (Trial 1), the administration of 40 mg/kg raxibacumab intravenously following ciprofloxacin intravenous infusion or ciprofloxacin oral tablet ingestion did not alter the PK of ciprofloxacin administered orally and/or intravenously. Likewise, ciprofloxacin did not alter the PK of raxibacumab [see Drug Interactions (7.1)].

Co-Administration with AVA Trial

The effect of a single 40 mg/kg infusion of raxibacumab on the immunogenicity of a three-dose regimen of AVA administered (SC) was assessed in an open-label randomized trial in healthy adult male and female subjects (Trial 4). The trial included two treatment arms. In the combination arm, the first dose of AVA was administered immediately following the raxibacumab infusion (Day 1), while the second and third doses were administered on Days 15 and 29. In the AVA-alone arm, these SC AVA doses were administered on Days 1, 15 and 29. Overall immune response to AVA in the combination arm was found to be similar to the AVA-alone arm.

12.4 Microbiology

Mechanism of Action

Raxibacumab is a monoclonal antibody that binds free PA with an affinity equilibrium dissociation constant (Kd) of 2.78 ± 0.9 nM. Raxibacumab inhibits the binding of PA to its cellular receptors, preventing the intracellular entry of the anthrax lethal factor and edema factor, the enzymatic toxin components responsible for the pathogenic effects of anthrax toxin.

Activity In Vitroand In Vivo

Raxibacumab binds in vitroto PA from the Ames, Vollum, and Sterne strains of B. anthracis. Raxibacumab binds to an epitope on PA that is conserved across reported strains of B. anthracis.

In vivostudies in rats suggest that raxibacumab neutralizes the toxicity due to lethal toxin, as animals slowly infused with lethal toxin (a combination of PA + lethal factor) survived 7 days following administration. The median time to death in control rats was 16 hours. Similar observations were noted in animal efficacy studies in rabbits and monkeys challenged with B. anthracisspores by the inhalational route. PA was detected in animals following exposure to B. anthracisspores. PA levels rose and then fell to undetectable levels in animals that responded to treatment and survived, whereas levels continued to rise in animals that failed treatment and died or were euthanized because of poor clinical condition [see Clinical Studies (14.1)].

13 NONCLINICAL TOXICOLOGY

13.1 Carcinogenesis, Mutagenesis, Impairment of Fertility

Carcinogenicity, genotoxicity, and fertility studies have not been conducted with raxibacumab.

13.2 Animal Toxicology

Healthy cynomolgus macaques administered 3 intravenous doses or 3 SC doses of 40 mg/kg raxibacumab once every 12 days, or a single intramuscular dose (40 mg/kg) of raxibacumab, showed no adverse effects, including no effects up to 120 days post-dosing.

Studies with raxibacumab in rabbit, cynomolgus macaque, and human donor tissues showed no cross reactivity with brain.

Anthrax-infected rabbits and monkeys administered an intravenous injection of raxibacumab (40 mg/kg) at time of PA toxemia reproducibly showed greater severity of central nervous system (CNS) lesions (bacteria, inflammation, hemorrhage, and necrosis) in non-surviving animals compared with dead placebo-control animals, with no difference in mean time to death from spore challenge. The raxibacumab monoclonal antibody appears unable to penetrate the CNS until compromise of the blood-brain barrier (BBB) during the later stages of anthrax infection. The most severe brain lesions in rabbits were associated with bacteria and raxibacumab tissue binding in a similar pattern as endogenous IgG antibody that leaked across the compromised BBB. No dose/exposure-response relationship for brain histopathology was identified. Surviving rabbits and monkeys at the end of the 28-day studies showed no microscopic evidence of CNS lesions. CNS toxicity was not observed in healthy monkeys administered raxibacumab (40 mg/kg) or in GLP combination treatment studies with antibacterials in rabbits (levofloxacin) or in monkeys (ciprofloxacin) at any time.

14 CLINICAL STUDIES

Because it is not feasible or ethical to conduct controlled clinical trials in humans with inhalational anthrax, the effectiveness of raxibacumab for therapeutic treatment of inhalational anthrax is based on efficacy studies in rabbits and monkeys. Raxibacumab effectiveness has not been studied in humans. Because the animal efficacy studies are conducted under widely varying conditions, the survival rates observed in the animal studies cannot be directly compared between studies and may not reflect the rates observed in clinical practice.

The efficacy of raxibacumab for treatment of inhalational anthrax was studied in a monkey model (Study 2) and a rabbit model (Studies 3 and 4) of inhalational anthrax disease. These 3 studies tested raxibacumab efficacy compared with placebo. Another study in a rabbit model (Study 1) evaluated the efficacy of raxibacumab in combination with an antibacterial drug relative to the antibacterial drug alone. Studies were randomized and blinded.

The animals were challenged with aerosolized B. anthracisspores (Ames strain) at 200 x LD50to achieve 100% mortality if untreated. In rabbit Study 1, treatment was delayed until 84 hours after spore challenge. In monkey Study 2, study treatment commenced at the time of a positive serum electrochemiluminescence (ECL) assay for B. anthracisPA. The mean time between spore challenge and initiation of study treatment was 42 hours. In rabbit Studies 3 and 4, sustained elevation of body temperature above baseline for 2 hours or a positive result on serum ECL assay for PA served as the trigger for initiation of study treatment. The mean time between spore challenge and initiation of study treatment was 28 hours post-exposure. Efficacy in all therapeutic studies in animals was determined based on survival at the end of the study. Most study animals (88% to 100%) were bacteremic and had a positive ECL assay for PA prior to treatment in all 4 studies.

14.1 Treatment of Inhalational Anthrax in Combination with Antibacterial Drug

The efficacy of raxibacumab administered with levofloxacin as treatment of animals with systemic anthrax disease (84 hours after spore challenge) was evaluated in New Zealand White rabbits (Study 1). The dose of levofloxacin was chosen to yield a comparable exposure to that achieved by the recommended doses in humans. Levofloxacin and raxibacumab PK in this study were unaffected by product co-administration. Forty-two percent of challenged animals survived to treatment. Treatment with antibacterial drug plus raxibacumab resulted in 82% survival compared with 65% survival in rabbits treated with antibacterial drug alone, P = 0.0874 (Table 5).

Table 5. Survival Rates in NZW Rabbits in Combination Therapy Study, All-Treated Animals
Treatment Group | NZW Rabbits (35 days)a Study 1
Treatment Group | Number (%) Survivors | PValueb | 95% CIc; Levofloxacin versus; Levofloxacin + Raxibacumab
Levofloxacin alone | 24/37 (65%) | - | -
Levofloxacin + Raxibacumab 40 mg/kg intravenous single dose | 32/39 (82%) | 0.0874 | (-2.4, 36.7)
aSurvival assessed 28 days after last dose of levofloxacin.
b Pvalue based on a two-sided likelihood ratio chi-square test.
c95% confidence interval based on normal approximation.

14.2 Post-Exposure Prophylaxis/Early Treatment of Inhalational Anthrax

Monkey Study 2 and rabbit Studies 3 and 4 evaluated treatment with raxibacumab alone at an earlier time point after exposure than rabbit Study 1. Treatment with raxibacumab alone resulted in a statistically significant dose-dependent improvement in survival relative to placebo when administered at the time of initial manifestations of anthrax disease in the rabbit and monkey infection models (Table 6). Raxibacumab at 40 mg/kg intravenous single dose was superior to placebo in the rabbit and monkey studies in the all-treated and the bacteremic animal analysis populations. All surviving animals developed toxin-neutralizing antibodies.

Table 6. Survival Rates in Animals Treated with Raxibacumab, All-Treated Animals
 | Cynomolgus Macaques at 28 Daysa Study 2 |  |  | NZW Rabbits at 14 Daysb Study 3 |  |  | NZW Rabbits at 28 Daysa Study 4
Treatment Group | Number (%) Survivors | PValuec | 95% CId | Number (%) Survivors | PValuec | 95% CId | Number (%) Survivors | PValuec | 95% CId
Placebo | 0/12 |  |  | 0/17 |  |  | 0/24
20 mg/kg raxibacumab | 7/14 (50%) | 0.0064 | (19.3, 73.7) | 5/18 (28%) | 0.0455 | (6.6, 52.5) | - | - | -
40 mg/kg raxibacumab | 9/14 (64%) | 0.0007 | (31.6, 84.7) | 8/18 (44%) | 0.0029 | (21.3, 66.7) | 11/24 (46%) | 0.0002 | (27.0, 66.1)
aSurvival measured at 28 days after spore challenge.
bSurvival measured at 14 days after spore challenge.
c Pvalue based on two-sided Fisher's exact test for comparisons between raxibacumab and placebo.
d95% CIs are exact confidence intervals for the difference between raxibacumab and placebo.

In other animal studies evaluating antibacterial drug alone and raxibacumab-antibacterial drug combination, the efficacy of an antibacterial drug alone (levofloxacin in rabbits and ciprofloxacin in monkeys) was very high (95% to 100%) when given at the initial manifestations of inhalational anthrax disease. The timing of treatment was similar to that reported for Studies 2, 3, and 4 above.

In another study, rabbits were exposed to 100 times LD50 B. anthracisspores and administered raxibacumab at a single dose of 40 mg/kg at the time of exposure, 12 hours, 24 hours, or 36 hours after exposure. Survival was 12/12 (100%) in animals treated at time of exposure or at 12 hours but decreased to 6/12 (50%) and 5/12 (42%) at 24 hours and 36 hours, respectively.

16 HOW SUPPLIED/STORAGE AND HANDLING

Raxibacumab is a sterile, preservative-free, clear to opalescent, colorless to pale yellow solution supplied in single-use vials containing 1,700 mg/34 mL (50 mg/mL) raxibacumab and is available in the following packaging configuration:

Single Unit Carton: Contains one single-use vial of raxibacumab 1,700 mg/34 mL (NDC 71655-103-01).

Raxibacumab must be refrigerated at 2°C to 8°C (36°F to 46°F). DO NOT FREEZE. Protect the vial from exposure to light, prior to use. Brief exposure to light, as with normal use, is acceptable. Store vial in original carton until time of use.

17 PATIENT COUNSELING INFORMATION

Advise the patient to read the FDA-approved patient labeling (Patient Information).

Efficacy Based on Animal Models

Inform patients that the efficacy of raxibacumab is based solely on efficacy studies demonstrating a survival benefit in animals and that the effectiveness of raxibacumab has not been tested in humans with anthrax. The safety of raxibacumab has been tested in healthy adults, but no safety data are available in children or pregnant women. Limited data are available in geriatric patients [see Use in Specific Populations (8.5)].

Hypersensitivity Reactions and Anaphylaxis

Inform patients that hypersensitivity reactions, including anaphylaxis, have occurred with the administration of raxibacumab. Inform patients of the signs and symptoms of hypersensitivity and anaphylaxis and instruct patients to seek immediate medical care if they experience such symptoms during or following administration of raxibacumab.

Prophylactic administration of diphenhydramine is recommended within 1 hour prior to administering raxibacumab to reduce the risk of occurrence and/or the severity of hypersensitivity reactions [see Warnings and Precautions (5.1)] .

Manufactured by
Emergent Manufacturing Operations Baltimore LLC
Baltimore, MD 21224
U.S. License No. 2083

Emergent BioSolutions Inc.

Any and all Emergent BioSolutions Inc. brand, product, service and feature names, logos and slogans are trademarks or registered trademarks of Emergent BioSolutions Inc. or its subsidiaries in the United States or other countries. All rights reserved.

PATIENT INFORMATION

RAXIBACUMAB (rack-see-BACK-u-mab)

Injection, for intravenous use

What is the most important information I should know about RAXIBACUMAB?
RAXIBACUMAB can cause serious side effects, including:

- Serious allergic reactions.Tell your healthcare provider right away if you have any of the following symptoms while receiving RAXIBACUMAB or after receiving RAXIBACUMAB:

- rash
- hives

- itching
- chills

- chest tightness or shortness of breath
- throat tightness or trouble breathing

- swelling of the lips, throat, or tongue
- feeling dizzy or lightheaded

What is RAXIBACUMAB?

- RAXIBACUMAB is a prescription medicine used along with antibiotic medicines to treat people with inhalational anthrax. RAXIBACUMAB can also be used to prevent inhalational anthrax disease when there are no other treatment options.
- The effectiveness of RAXIBACUMAB has been studied only in animals with inhalational anthrax. There have been no studies in people who have inhalational anthrax.
- The safety of RAXIBACUMAB was studied in healthy adults. There have been no studies of RAXIBACUMAB in pediatric patients.
- RAXIBACUMAB is not used for prevention or treatment of anthrax meningitis.

Before you receive RAXIBACUMAB, tell your healthcare provider about all of your medical conditions, including if you are:

- allergic to any of the ingredients in RAXIBACUMAB. See the end of this leaflet for a list of the ingredients in RAXIBACUMAB.
- allergic to diphenhydramine (BENADRYL).
- pregnant or planning to become pregnant. It is not known if RAXIBACUMAB will harm your unborn baby.
- breastfeeding or plan to breastfeed. It is not known if RAXIBACUMAB passes into your breast milk. You and your healthcare provider should decide if you will receive RAXIBACUMAB or breastfeed.

Tell your healthcare provider about all the medicines you take, including prescription and over-the-counter medicines, vitamins, and herbal supplements.

How will I receive RAXIBACUMAB?

- You will be given 1 dose of RAXIBACUMAB by a healthcare provider through a vein (intravenous infusion). It takes about 2 hours and 15 minutes to give you the full dose of medicine.
- Your healthcare provider should give you a medicine called diphenhydramine (BENADRYL) before you receive RAXIBACUMAB to help reduce your chances of developing an allergic reaction from RAXIBACUMAB. BENADRYL may be given to you to take by mouth or through a vein.
- BENADRYL may make you sleepy, and you should use caution if you will be driving or operating equipment.

What are the possible side effects of RAXIBACUMAB?

RAXIBACUMAB can cause serious side effects, including:

- See “ What is the most important information I should know about RAXIBACUMAB?”

The most common side effects of RAXIBACUMAB include:

- rash
- pain in your arms or legs
- itchiness

- sleepiness
- injection site reactions, including redness and pain
- headache

Tell your healthcare provider if you have any side effect that bothers you or that does not go away. These are not all the possible side effects of RAXIBACUMAB. For more information, ask your healthcare provider.

Call your doctor for medical advice about side effects.

You may report side effects to FDA at 1-800-FDA-1088. For more information go to dailymed.nlm.nih.gov.

General information about the safe and effective use of RAXIBACUMAB.

Medicines are sometimes prescribed for purposes other than those listed in a patient information leaflet. This patient information leaflet summarizes the most important information about RAXIBACUMAB. If you would like more information, talk to your healthcare provider. You can ask your pharmacist or healthcare provider for information about RAXIBACUMAB that is written for health professionals.

What are the ingredients in RAXIBACUMAB?

Active ingredient:raxibacumab

Inactive ingredients:citric acid, glycine, polysorbate 80, sodium citrate, sucrose, Water for Injection.

Manufactured by Emergent Manufacturing Operations Baltimore LLC

Baltimore, MD 21224

U.S. License No. 2083

Emergent BioSolutions Inc.

For more information, go to www.emergentbiosolutions.com or call 1-800-768-2304.

BENADRYL is a trademark owned by or licensed to its owner and is not owned by or licensed to the Emergent group of companies. The maker of this brand is not affiliated with and does not endorse the Emergent group of companies or its products.

Any and all Emergent BioSolutions Inc. brand, product, service and feature names, logos and slogans are trademarks or registered trademarks of Emergent BioSolutions Inc. or its subsidiaries in the United States or other countries. All rights reserved.

This Patient Information has been approved by the U.S. Food and Drug Administration. Revised: 6/2021

PACKAGE LABEL

PRINCIPAL DISPLAY PANEL

NDC 71655-103-01

Raxibacumab

Injection

1700 mg/34 mL

(50 mg/mL)

For Intravenous Infusion

Must be Diluted Prior To Use

Rx only

Single-Use Vial; Discard unused portion.

34 mL

PACKAGE LABEL

PRINCIPAL DISPLAY PANEL

NDC 71655-103-01

Raxibacumab

Injection

1700 mg/34 mL

(50 mg/mL)

For Intravenous Infusion

Must be Diluted Prior To Use

Rx only

Single-Use Vial

Discard unused portion.

34 mL

See prescribing information for dilution and dosage information.

REFRIGERATE: Store at 2° to 8°C (36° to 46°F).

Do Not Freeze.

Protect From Lightby storing in original package until use.

Manufactured by Emergent Manufacturing Operations Baltimore LLC, Baltimore, MD 21224

U.S. License No. 2083

Rev. 6/18

62000000024963